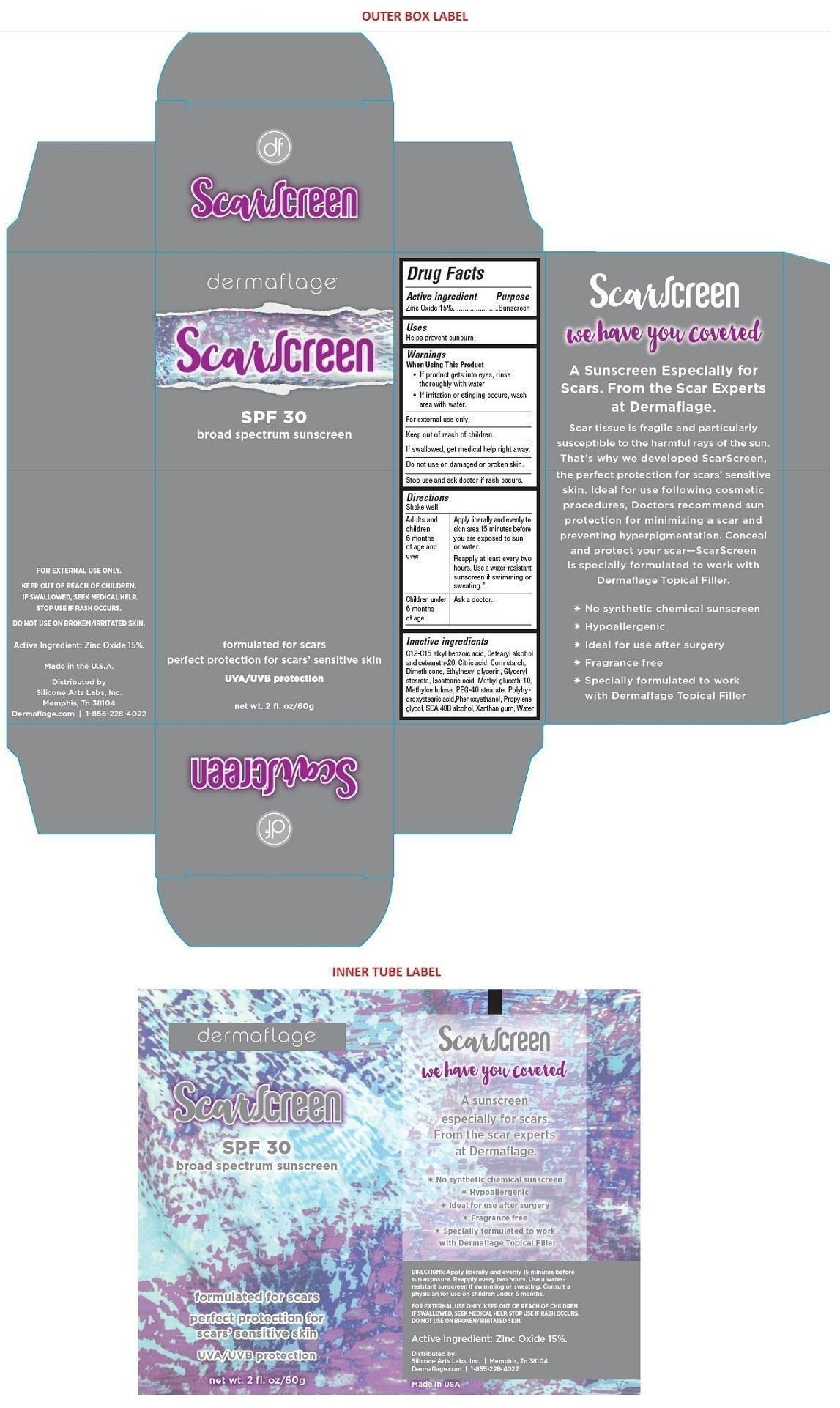 DRUG LABEL: ScarScreen
NDC: 70089-100 | Form: LOTION
Manufacturer: Natural Crest Laboratories Inc.
Category: otc | Type: HUMAN OTC DRUG LABEL
Date: 20150915

ACTIVE INGREDIENTS: ZINC OXIDE 0.75 g/5 mL
INACTIVE INGREDIENTS: ALKYL (C12-15) BENZOATE; CETOSTEARYL ALCOHOL; POLYOXYL 20 CETOSTEARYL ETHER; ANHYDROUS CITRIC ACID; STARCH, CORN; DIMETHICONE 200; ETHYLHEXYLGLYCERIN; GLYCERYL MONOSTEARATE; ISOSTEARIC ACID; METHYL GLUCETH-10; METHYLCELLULOSE (4000 MPA.S); PEG-40 STEARATE; POLYHYDROXYSTEARIC ACID (2300 MW); PHENOXYETHANOL; PROPYLENE GLYCOL; ALCOHOL; XANTHAN GUM; WATER

ScarScreen

Active Ingredient

Zinc Oxide 15%

Purpose

Sunscreen

Keep out of reach of children.

Uses

Helps prevent sunburn.

Warnings

When Using This Product

- If product gets into eyes, rinse thoroughly with water
- If irritation or stinging occurs, wash area with water

For external use only.

If swallowed, get medical help right away.

Do not use on damaged or broken skin.

Stop use and ask doctor if rash occurs.

Directions

Shake Well

Adults and children 6 months of age and over | Apply liberally and evenly to skin area 15 minutes before you are exposed to sun or water.; Reapply at least every two hours. Use a water-resistant sunscreen if swimming or sweating.”
Children under 6 months of age | Ask a doctor

Consult a physician for use on children under 6 months.

Inactive ingredients

C12-C15 alkyl benzoic acid, Cetearyl alcohol and ceteareth-20, Citric acid, Corn starch, Dimethicone, Ethylhexyl glycerin, Glyceryl stearate, Isostearic acid, Methyl gluceth-10, Methylcellulose, PEG-40 stearate, Polyhydroxystearic acid, Phenoxyethanol, Propylene glycol, SDA 40B alcohol, Xanthan gum, Water

SPF 30

broad spectrum sunscreen

formulated for scars

perfect protection for scars' sensitive skin

UVA/UVB protection

A Sunscreen Especially for Scars. From the Scar Experts at Dermaflage.

Scar tissue is fragile and particularly susceptible to the harmful rays of the sun. That's why we developed ScarScreen, the perfect protection for scars' sensitive skin. Ideal for use following cosmetic procedures, Doctors recommend sun protection for minimizing a scar and preventing hyperpigmentation. Conceal and protect your scar-ScarScreen is specially formulated to work with Dermaflage Topical Filler.

* No synthetic chemical sunscreen

* Hypoallergenic

* Ideal for use after surgery

* Fragrance free

* Specially formulated to work with Dermaflage Topical Filler

Made in the U.S.A.

Distributed by

Silicone Arts Labs, Inc.

Memphis, Tn 38104

Dermaflage.com | 1-855-228-4022